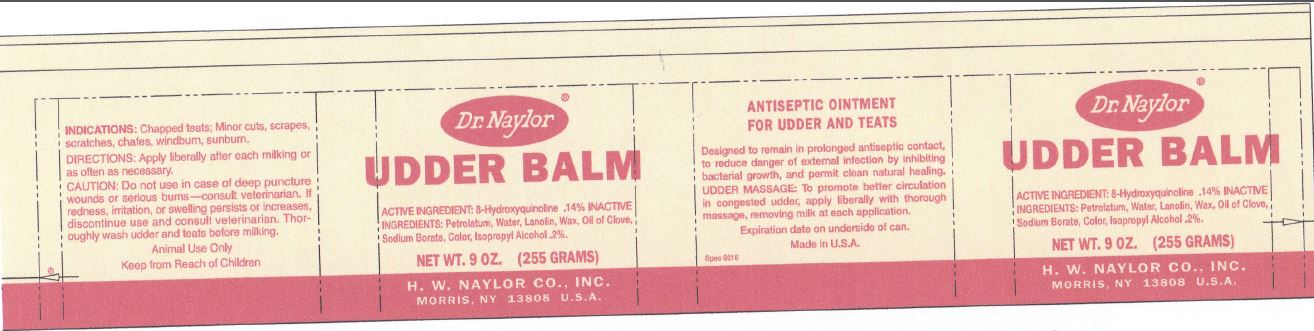 DRUG LABEL: UDDER BALM 
NDC: 15878-413 | Form: OINTMENT
Manufacturer: H. W. Naylor Company Inc.
Category: animal | Type: OTC ANIMAL DRUG LABEL
Date: 20130104

ACTIVE INGREDIENTS: Oxyquinoline .25 g/1 g
INACTIVE INGREDIENTS: Petrolatum; Water; Lanolin; Yellow Wax; Paraffin; Clove Leaf Oil; Sodium Borate; Apocarotenal; .beta.-carotene; Isopropyl Alcohol

UDDER BALM

Active Ingredients

8-Hydroxyquinoline .14%

Purpose

Chapped teats, Minor cuts, scrapes, scratches, chafes, windburn, sunburn.

Directions

Apply liberally after each milking or as often as necessary.

Safety

CAUTION: Do not use in case of deep puncture wounds or serious burns – consult veterinarian.

If redness, irritation or swelling persists or increases, discontinue use and consult veterinarian.

Thoroughly wash udder and teats before milking.

Animal Use Only

Other Ingredients

Petrolatum, Water, Lanolin, Wax, Oil of Clove, Sodium Borate, Color, Isopropyl Alcohol .2%.

Questions?

H. W. NAYLOR CO., INC.
MORRIS, NY 13808 U.S.A.

Principal Display Panel

Dr. Naylor®
UDDER BALM
NET WT. 9 OZ. (255 GRAMS)
H.W. NAYLOR CO., INC.
MORRIS, NY 13808 U.S.A.
ANTISEPTIC OINTMENT FOR UDDER AND TEATS
Designed to remain in prolonged antiseptic contact, to reduce danger of external infection by inhibiting bacterial growth, and permit clean natural healing.
UDDER MASSAGE: To promote better circulation in congested udder, apply liberally with thorough massage, removing milk at each application.
Expiration date on underside of can.
Made in U.S.A.
Spec 6016